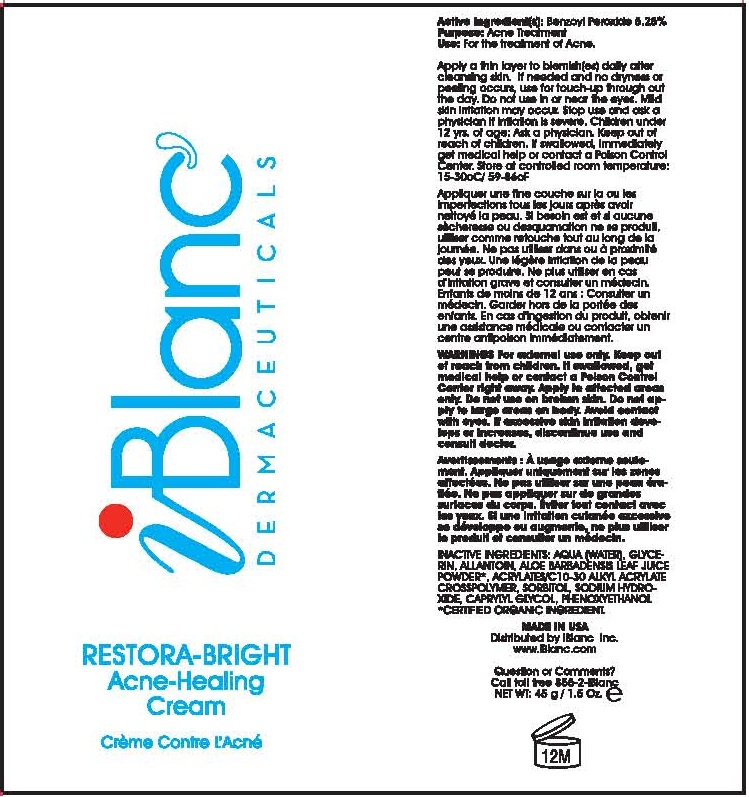 DRUG LABEL: iBlanc Restora-Bright
NDC: 52960-101 | Form: CREAM
Manufacturer: iBlanc Inc.
Category: otc | Type: HUMAN OTC DRUG LABEL
Date: 20120818

ACTIVE INGREDIENTS: Benzoyl Peroxide 5.3 g/100 g
INACTIVE INGREDIENTS: Water; Glycerin; Allantoin; ALOE VERA LEAF; Carbomer Copolymer TYPE A; Sorbitol; Sodium Hydroxide; Caprylyl Glycol; Phenoxyethanol

iBlanc Restora-Bright Acne-Healing Cream

INDICATIONS AND USAGE

USES: FOR THE TREATMENT OF ACNE

Active Ingredient: Benzoyl Peroxide 5.25%

Uses

- for the treatment of acne

Warnings

For external use only

When using this product

- skin irritation and dryness is more likely to occur if you use another topical acne medication at the same time. If irritation occurs, only use one topical acne medication at a time.

Do not use if you

- have very sensitive skin.
- are sensitive to benzoyl peroxide

When using this product

- avoid unnecessary skin exposure and use a sunscreen
- avoid contact with eyes, lips and mouth. If eye contact accidentally occurs, rinse eyes throughly with water.
- avoid contact with hair and dyed fabrics which may be bleached by this product
- skin irritation may occur, characterized by redness, burning, itching, peeling, or possibly swelling. Irritation may be reduced by using the product less frequently or in a lower concentration.

Stop use and ask a doctor if irritation becomes severe.

INACTIVE INGREDIENT

Inactive Ingredients Aqua (Water), Glycerin, Allantoin, Aloe Barbadensis Leaf Juice Powder, Acrylates/C13-30 Alkyl Acrylate Crosspolymer, Sorbitol, Sodium Hydroxide, Caprylyl Glycol, Phenoxyethanol

Keep out of reach of children. If swallowed, get medical help or contact a Poison Control Center immediately.

PACKAGE LABEL

iBlanc Dermaceuticals
RESTORA-BRIGHT
ACNE-HEALING
CREAM

DOSAGE AND ADMINISTRATION

APPLY A THIN LAYER TO BLEMISHES DAILY AFTER CLEANSING SKIN. IF NEEDED AND NO DRYNESS OR PEELING OCCURS, USE FOR TOUCH-UP THROUGHOUT THE DAY.